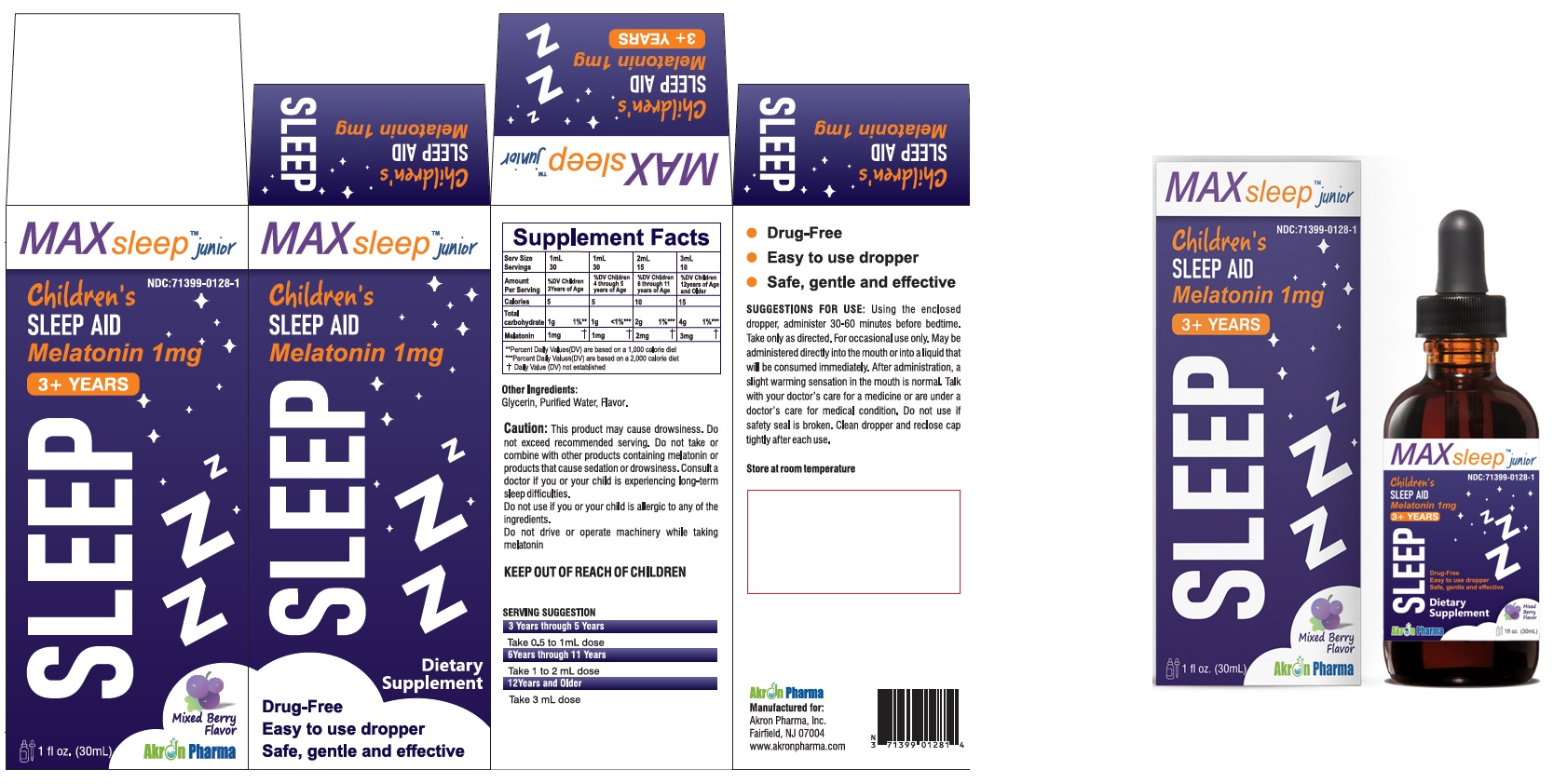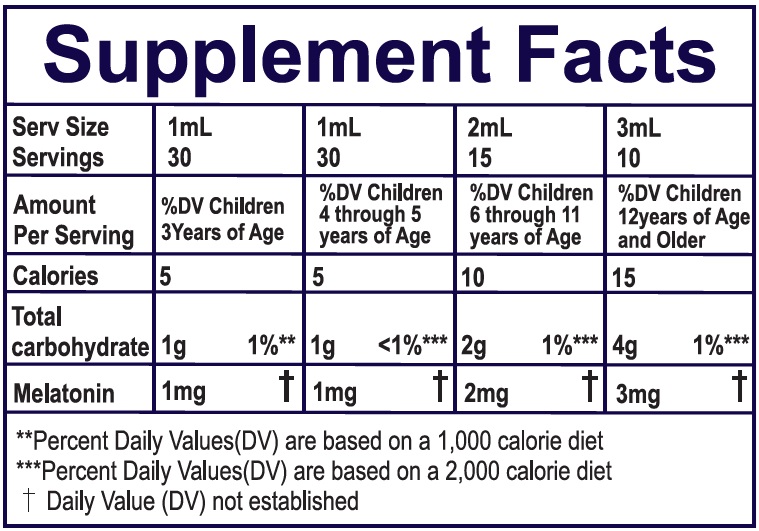 DRUG LABEL: MAX Sleep Junior Childrens SLEEP AID
NDC: 71399-0128 | Form: SOLUTION/ DROPS
Manufacturer: Akron Pharma
Category: other | Type: DIETARY SUPPLEMENT
Date: 20240623

ACTIVE INGREDIENTS: MELATONIN 1 mg/1 mL
INACTIVE INGREDIENTS: GLYCERIN; WATER

MAX Sleep Junior
Childrens SLEEP AID
Melatonin 1 mg

HEALTH CLAIM

- Drug-Free
- Easy to use dropper
- Safe, gentle and effective

* This statement has not been evaluated by the Food and Drug Administration. This product is not intended to diagnose, treat, cure, or prevent any disease.

SAFE HANDLING WARNING

Store at room temperature

WARNINGS

Caution: This product may cause drowsiness. Do not exceed recommended serving. Do not take or combine with other products containing melatonin or products that cause sedation or drowsiness. Consult a doctor if you or your child is experiencing long-term sleep difficulties.
Do not use if you or your child is allergic to any of the ingredients.

PRECAUTIONS

Do not drive or operate machinery while taking melatonin

DOSAGE AND ADMINISTRATION

SUGGESTIONS FOR USE: Using the enclosed dropper, administer 30-60 minutes before bedtime.
Take only as directed. For occasional use only. May be administered directly into the mouth or into a liquid that will be consumed immediately. After administration, a slight warming sensation in the mouth is normal. Talk with your doctor's care for a medicine or are under a doctor's care for medical condition. Do not use if safety seal is broken. Clean dropper and reclose cap tightly after each use.

Manutactured lor:
Akron Pharma, Inc.
Fairtield, NJ 07004
www.akronpharma.com